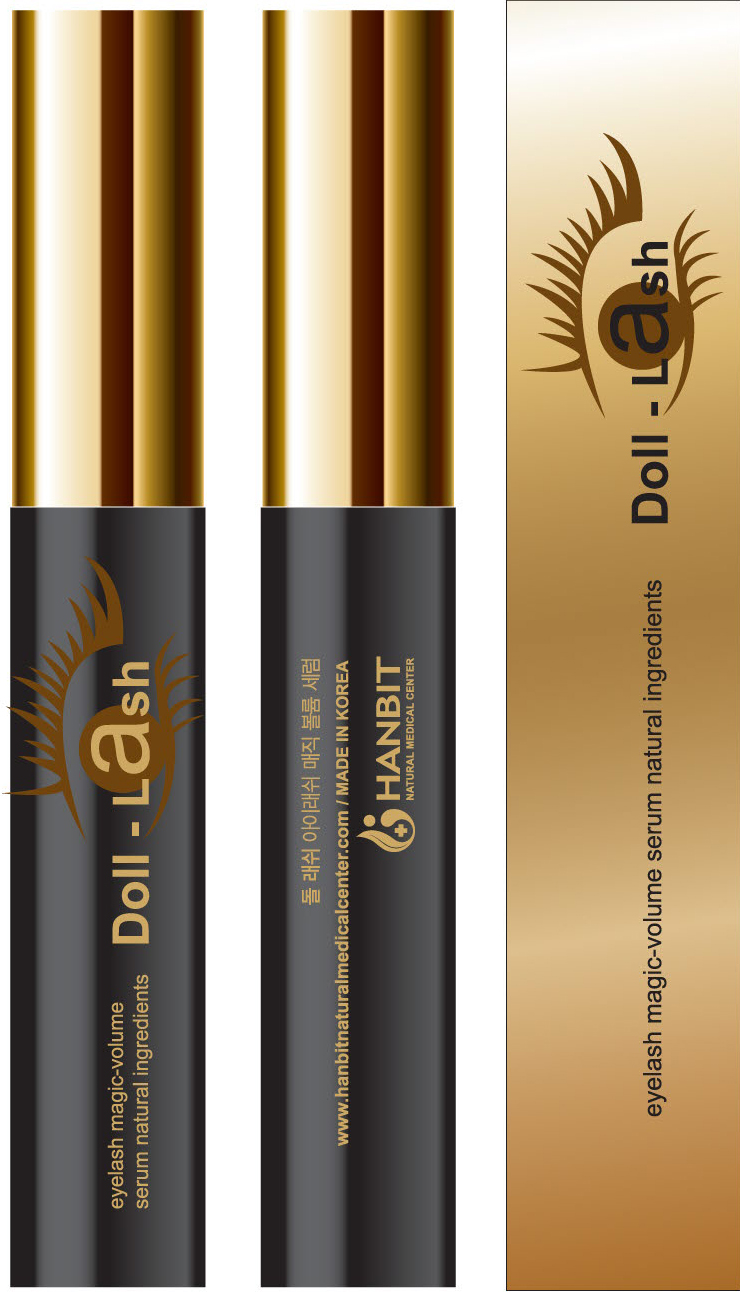 DRUG LABEL: Doll Lash
NDC: 51329-1001 | Form: LIQUID
Manufacturer: Hanbit Korea
Category: otc | Type: HUMAN OTC DRUG LABEL
Date: 20101106

ACTIVE INGREDIENTS: PYRITHIONE ZINC 2 mL/100 mL; PANTHENOL 0.5 mL/100 mL; NIACINAMIDE 0.3 mL/100 mL; BIOTIN 0.06 mL/100 mL
INACTIVE INGREDIENTS: ACORUS CALAMUS ROOT; ARTEMISIA ABSINTHIUM FLOWERING TOP; METHYLPARABEN; DIAZOLIDINYL UREA; WATER

Drug Facts

Active ingredient: Zinc pyrithione, Panthenol, Niacinamide, Biotin

Inactive ingredient: Acorus Calamus Root extract, Artemisia Absinthium extract, Methylparaben, thuja orientalis extract, Canavalia goadiata seed extract, Diazolidinyl urea

PURPOSE

For hair grower and loss prevention

KEEP OUT OF REACH OF CHILDREN

Keep this product out of the reach of children

INDICATIONS AND USAGE

Directions for use: Apply six~seven times daily and every night onto clean skin.

For best results, use as often as possible.

It can be use in makeup

WARNINGS

1.When using Doll-Lash, avoid direct contact with the eyes, mucous membranes and open wounds.

2. If redness or imitation occurs, discontinue use and consult with your physician.

3. Keep this product out of the reach of children.

DOSAGE AND ADMINISTRATION

Doll-Lash, Natural and vegetable property Eyelash , is our cosmetics product that enables short, weak, and thine eyelashes to be long, rich, healthy